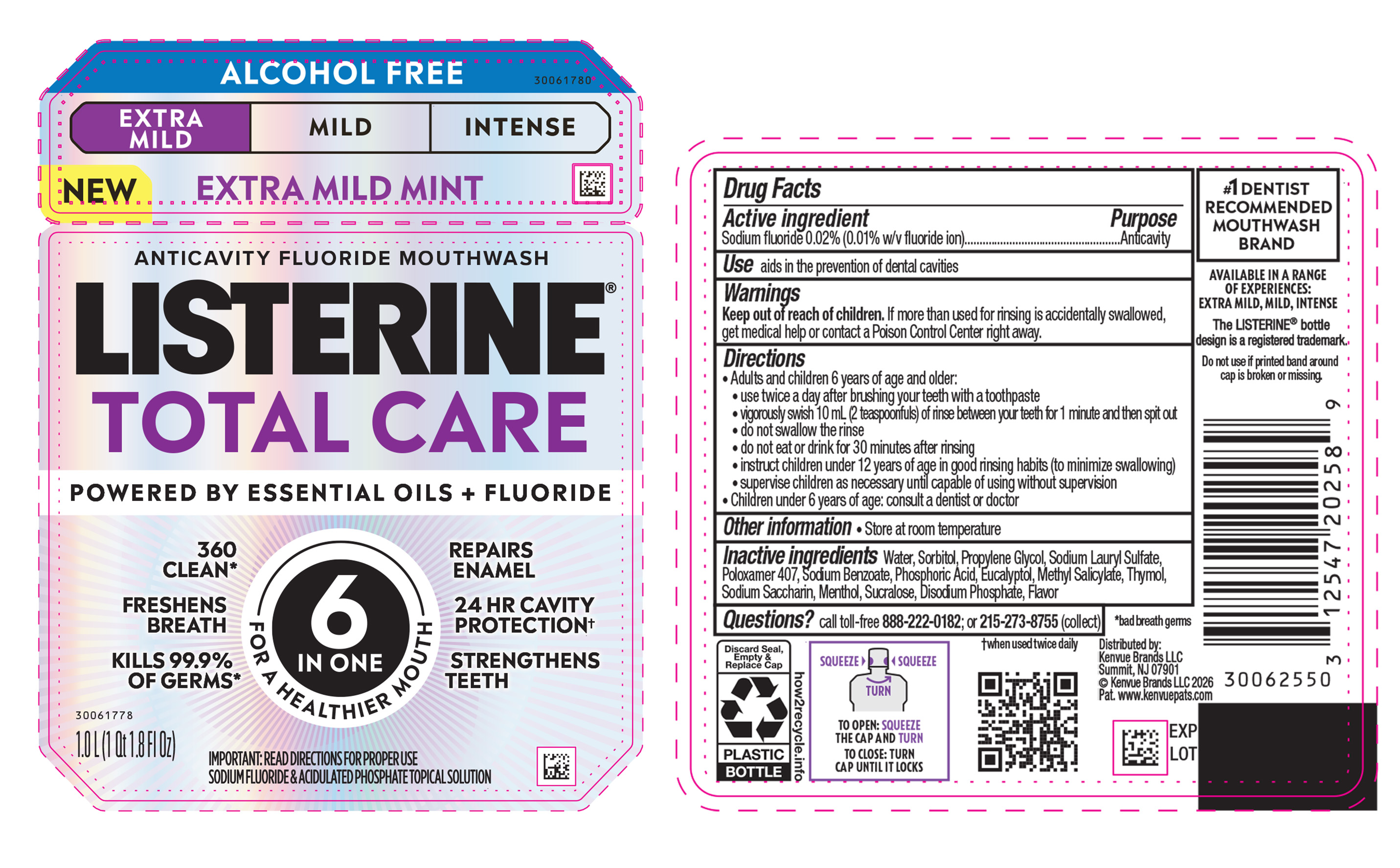 DRUG LABEL: Listerine Total Care Extra Mild Alcohol Free Anticavity Fluoride Mouthwash
NDC: 69968-0950 | Form: MOUTHWASH
Manufacturer: Kenvue Brands LLC
Category: otc | Type: HUMAN OTC DRUG LABEL
Date: 20260202

ACTIVE INGREDIENTS: SODIUM FLUORIDE 0.1 mg/1 mL
INACTIVE INGREDIENTS: WATER; SORBITOL; EUCALYPTOL; PROPYLENE GLYCOL; SODIUM LAURYL SULFATE; POLOXAMER 407; SODIUM BENZOATE; PHOSPHORIC ACID; METHYL SALICYLATE; THYMOL; SACCHARIN SODIUM; SUCRALOSE; MENTHOL; DISODIUM PHOSPHATE

Listerine Total Care Extra Mild Alcohol Free Anticavity Fluoride Mouthwash

Drug Facts

Active ingredient

Sodium Fluoride 0.02% (0.01% w/v Fluoride ion)

Purpose

Anticavity

Use

aids in the prevention of dental cavities

Warnings

Keep out of reach of children. If more than used for rinsing is accidentally swallowed, get medical help or contact a Poison Control Center right away.

Directions

- Adults and children 6 years of age and older:
  - use twice daily after brushing your teeth with a toothpaste
  - vigorously swish 10 mL (2 teaspoonfuls) of rinse between your teeth for 1 minute and then spit out
  - do not swallow the rinse
  - do not eat or drink for 30 minutes after rinsing
  - instruct children under 12 years of age in good rinsing habits (to minimize swallowing)
  - supervise children as necessary until capable of using without supervision
- Children under 6 years of age: consult a dentist or doctor

Other information

- store at room temperature

Inactive Ingredients

Water, Sorbitol, Propylene Glycol, Sodium Lauryl Sulfate, Poloxamer 407, Sodium Benzoate, Phosphoric Acid, Eucalyptol, Methyl Salicylate, Thymol,Sodium Saccharin, Menthol, Sucralose, Disodium Phosphate, Flavor

Questions?

call toll-free 888-222-0182 or 215-273-8755 (collect)

Distributed by:

Kenvue Brands LLC

Summit, NJ 07901

PRINCIPAL DISPLAY PANEL - 1000 mL Bottle Label

ANTICAVITY FLUORIDE MOUTHWASH

LISTERINE®

TOTAL CARE

POWERED BY ESSENTIAL OILS + FLUROIDE

6

IN 1

FOR A HEALTHIER MOUTH

360

CLEAN*

FRESHENS

BREATH

KILLS 99.9%

OF GERMS*

REPAIRS

ENAMEL

24 HR CAVITY

PROTECTION†

STRENGTHENS

TEETH

IMPORTANT: READ DIRECTIONS FOR PROPER USE

SODIUM FLUORIDE & ACIDULATED PHOSPHATE TOPICAL SOLUTION

1.0 L (1 Qt 1.8 FL Oz)